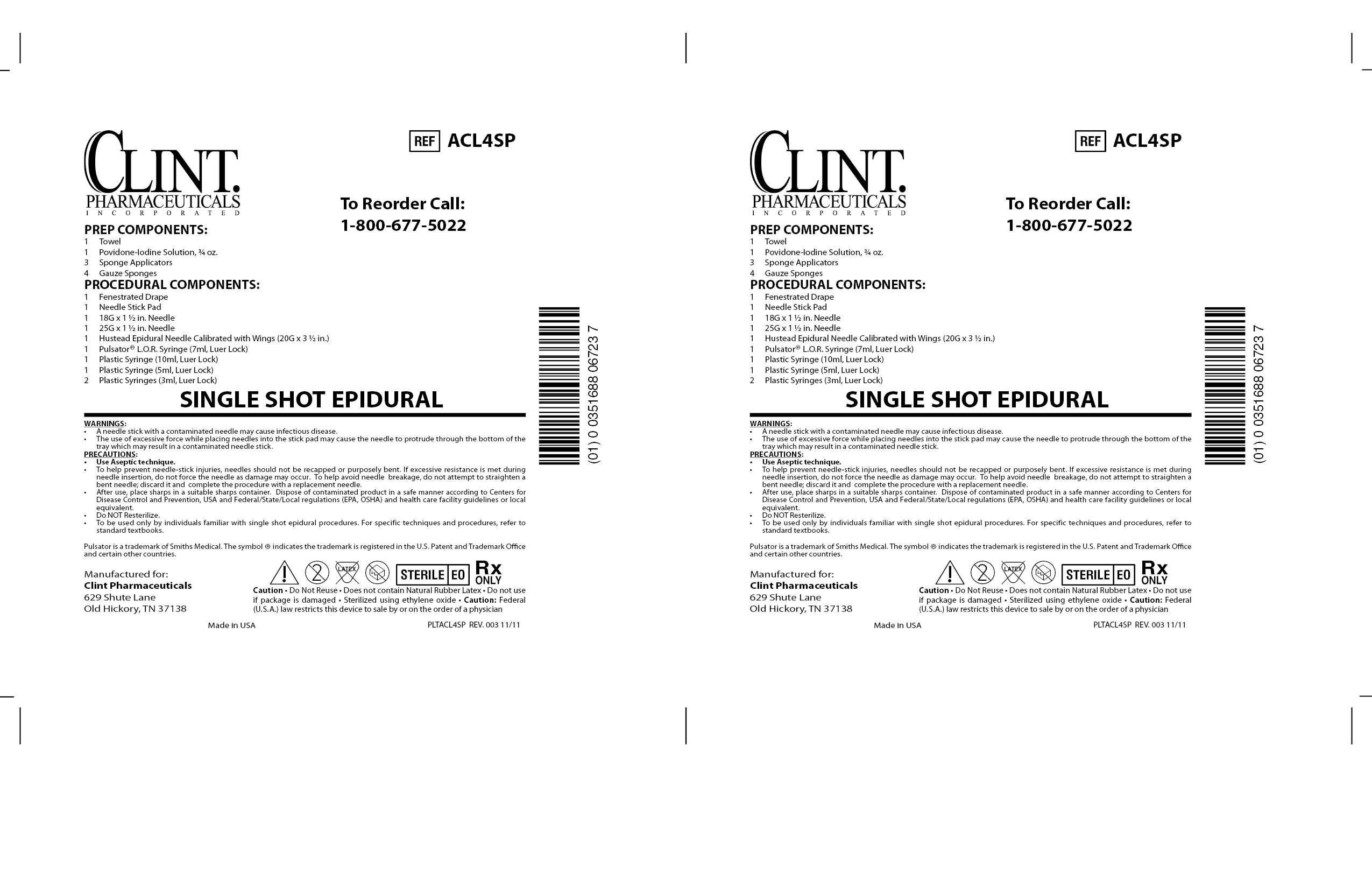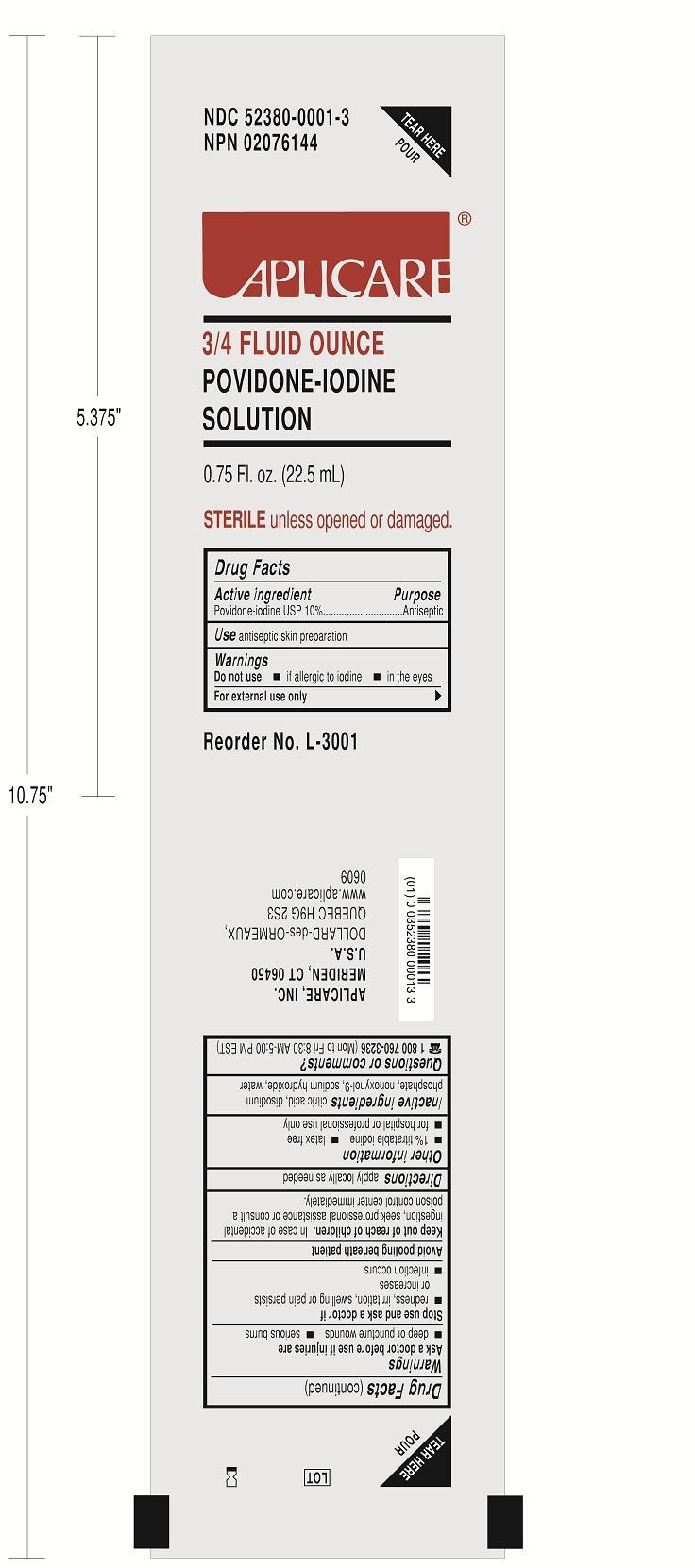 DRUG LABEL: ACL4SP SINGLE SHOT EPIDURAL
NDC: 55553-445 | Form: KIT | Route: TOPICAL
Manufacturer: Clint Pharmaceuticals, Inc.
Category: other | Type: MEDICAL DEVICE
Date: 20150401

ACTIVE INGREDIENTS: POVIDONE-IODINE 10 mg/1 mL
INACTIVE INGREDIENTS: CITRIC ACID MONOHYDRATE; SODIUM PHOSPHATE, DIBASIC; SODIUM HYDROXIDE; NONOXYNOL-9; WATER

Drug Facts

Povidone-iodine

PURPOSE

Antiseptic

Antiseptic skin preparation

Do not use

-if allergic to iodine

-in the eyes

For external use only

Ask a doctor before use if injuries are

-deep or puncture wounds

-serious burns

Stop use and ask a doctor if

-redness, irritation, swelling or pain persists or increases

-infection occurs

Avoid pooling beneath patient

Avoid excessive heat. Store at room temperature.

Keep out of reach of children

In case of accidental ingestion, seek professional assistance or consult a poison control center immediately.

INSTRUCTIONS FOR USE

Apply locally as needed.

OTHER SAFETY INFORMATION

1% titratable iodine latex free for hospital or professional use only

INACTIVE INGREDIENT

citric acid, disodium phosphate, nonoxynol-9, sodium hydroxide, water

QUESTIONS

1 800 760-3236 (Mon to Fri 8:30 AM-5:00 PM EST)

Package Label Display Panel